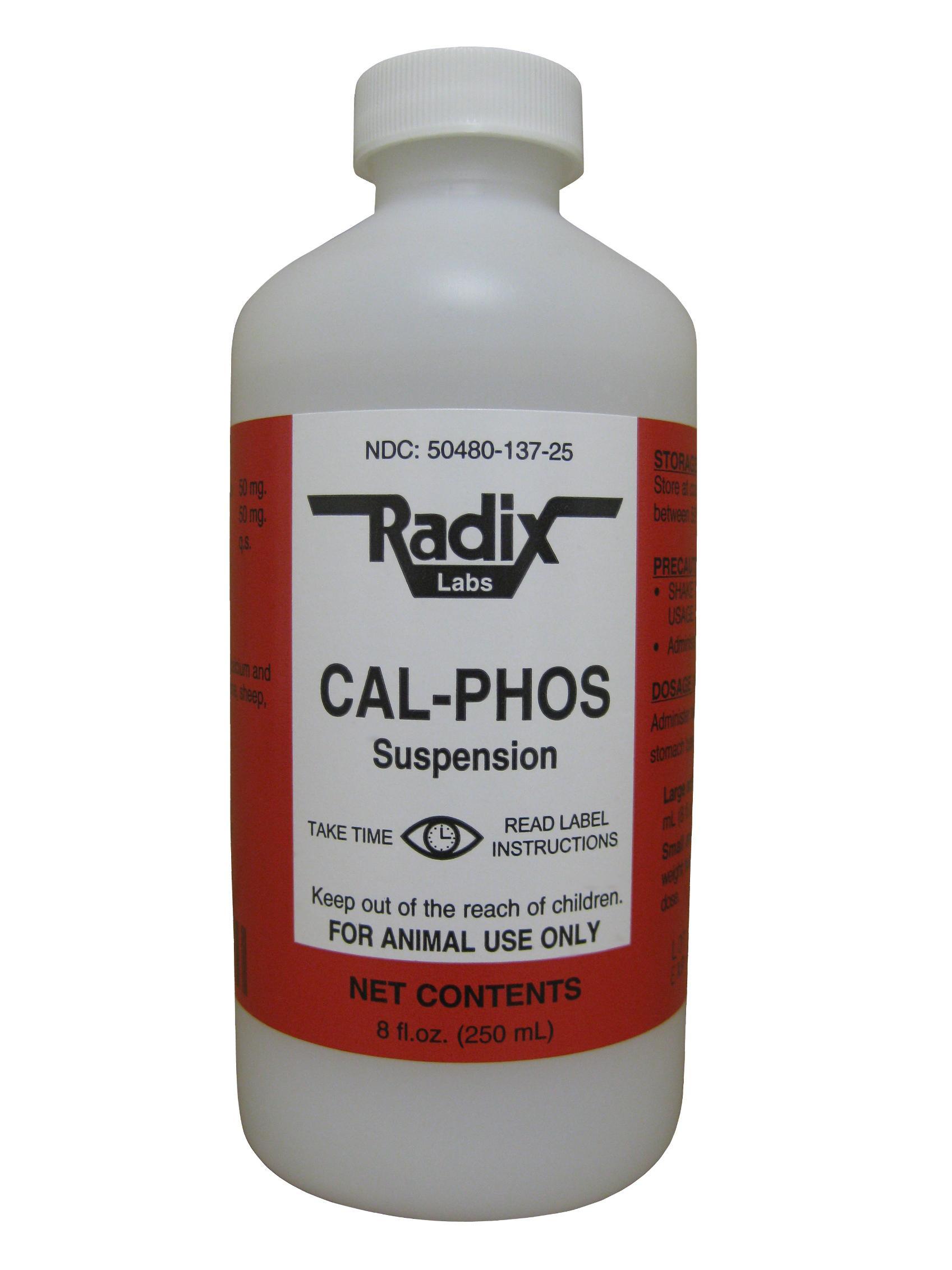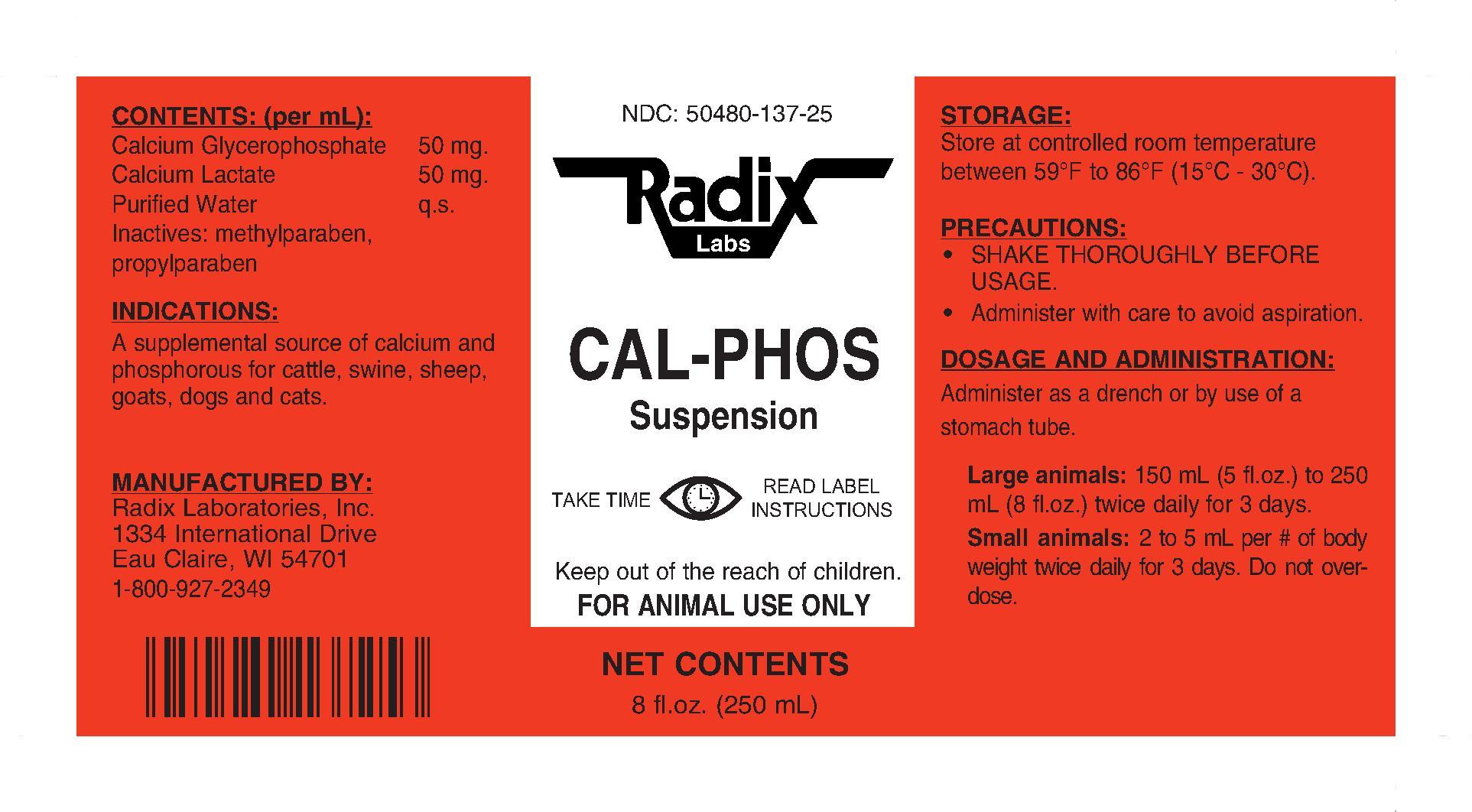 DRUG LABEL: CAL-PHOS SUSPENSION
NDC: 50480-137 | Form: LIQUID
Manufacturer: Radix Laboratories, Inc.
Category: animal | Type: OTC ANIMAL DRUG LABEL
Date: 20140325

ACTIVE INGREDIENTS: CALCIUM GLYCEROPHOSPHATE 12.5 g/250 mL; CALCIUM LACTATE 12.5 g/250 mL

CAL-PHOS SUSPENSION

• CONTENTS (per ml):

- Calcium Glycerophosphate .............50mg
- Calcium Lactate ..............................50mg

Inactives:

- Purified Water q.s.
- Inactives: Methylparaben, Propylparaben

Indications:

- For use as a supplemental source of calcium and phosphorus for cattle, swine, sheep, goats, dogs, and cats.

Storage:

- Store at controlled room temperature between 59oF to 86oF (15oC -30oC).

Warnings:

- SHAKE WELL BEFORE USAGE.
- Administer with care to avoid aspiration.

Dosage and administration:

- Administer orally as a drench or by use of a stomach tube.
- Large animals: 150mL (5 fl. oz.) to 250mL (8 fl. oz.) twice daily for 3 days.
- Small animals: 2 to 5 mL per # of body weight twice daily for 3 days.
- Do not overdose.

- Keep away from children.
- FOR ANIMAL USE ONLY